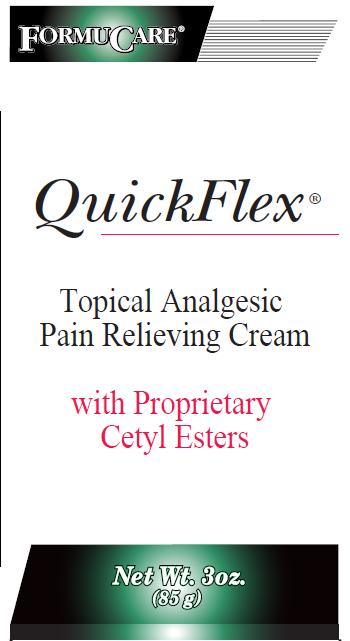 DRUG LABEL: QuickFlex
NDC: 10056-135 | Form: CREAM
Manufacturer: Access Business Group International LLC
Category: otc | Type: HUMAN OTC DRUG LABEL
Date: 20100725

ACTIVE INGREDIENTS: MENTHOL 1.25 g/100 g
INACTIVE INGREDIENTS: ALOE VERA LEAF; CETYL ALCOHOL; CINNAMON OIL; EUCALYPTUS OIL; GLYCERYL MONOSTEARATE; HYPROMELLOSE; PEPPERMINT OIL; POTASSIUM SORBATE; WATER; SQUALANE; STEARIC ACID; STEARYL ALCOHOL; GLYCERIN; GRAPE SEED OIL; JOJOBA OIL; TEA TREE OIL; METHYL SALICYLATE; CETYL ESTERS WAX

Active Ingredient

Menthol 1.25%

Purpose

Pain relieving cream

Use

Temporarily relieves minor aches and pains of muscles
and joints associated with:
simple backache
arthritis
strains
bruises
sprains

Warnings

For external use only

Do not use

on wounds or damaged skin

When using this product

- avoid contact with eyes or mucous membranes
- do not bandage tightly

Stop use and ask a doctor if

- condition worsens or symptoms persist for more than 7 days
- symptoms clear up and occur again within a few days

Directions

- Adult and children 2 years of age and older: Apply to affected area not more than 3 to 4 times daily.
- Children under 2 years of age: consult a physician.

Inactive Ingredients

aloe vera gel, cetyl alcohol, cetyl esters, cinnamon oil, eucalyptus oil, glyceryl stearate, grape seed oil, hypromellose, jojoba oil, peppermint oil, potassium sorbate, purified water, squalane, stearic acid, stearyl alcohol, tea tree oil, vegetable glycerin, wintergreen oil.

PACKAGE LABEL

Image of the principal display panel